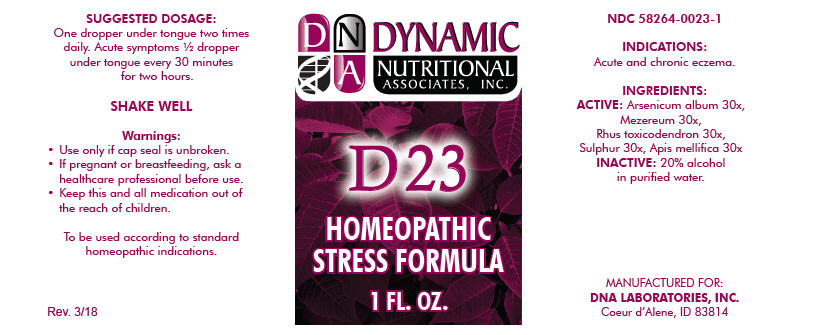 DRUG LABEL: D-23
NDC: 58264-0023 | Form: SOLUTION/ DROPS
Manufacturer: DNA Labs, Inc.
Category: homeopathic | Type: HUMAN OTC DRUG LABEL
Date: 20250113

ACTIVE INGREDIENTS: ARSENIC TRIOXIDE 30 [hp_X]/1 mL; DAPHNE MEZEREUM BARK 30 [hp_X]/1 mL; TOXICODENDRON PUBESCENS LEAF 30 [hp_X]/1 mL; SULFUR 30 [hp_X]/1 mL; APIS MELLIFERA 30 [hp_X]/1 mL
INACTIVE INGREDIENTS: WATER; ALCOHOL

D-23

NDC 58264-0023-1

INDICATIONS

PURPOSE

Acute and chronic eczema.

INGREDIENTS

ACTIVE

Arsenicum album 30x, Mezereum 30x, Rhus toxicodendron 30x, Sulphur 30x, Apis mellifica 30x

INACTIVE

20% alcohol in purified water.

SUGGESTED DOSAGE

One dropper under tongue two times daily. Acute symptoms ½ dropper under tongue every 30 minutes for two hours.

STORAGE AND HANDLING

SHAKE WELL

Warnings

- Use only if cap seal is unbroken.

PREGNANCY OR BREAST FEEDING

- If pregnant or breastfeeding, ask a healthcare professional before use.

KEEP OUT OF REACH OF CHILDREN

- Keep this and all medication out of the reach of children.

To be used according to standard homeopathic indications.

PRINCIPAL DISPLAY PANEL - 1 FL. OZ. Bottle Label

DYNAMIC
NUTRITIONAL
ASSOCIATES, INC.

D 23

HOMEOPATHIC
STRESS FORMULA

1 FL. OZ.